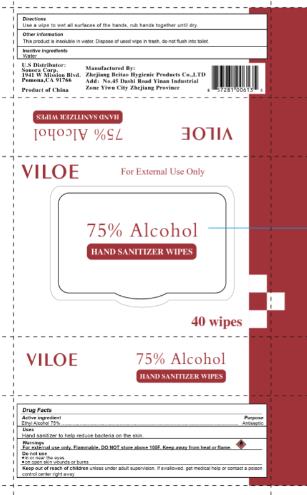 DRUG LABEL: Wet Wipe
NDC: 76906-007 | Form: SWAB
Manufacturer: Zhejiang BeiTao Hygienic Products Co., Ltd.
Category: otc | Type: HUMAN OTC DRUG LABEL
Date: 20211217

ACTIVE INGREDIENTS: ALCOHOL 75 g/100 g
INACTIVE INGREDIENTS: WATER

76906-007 wet wipes 75% Alcohol

Active Ingredient

Ethanol 75%

Purpose

Antiseptice Handwash

USE

For hand washing to decrease bacteria on the skin.
Recommended for repeated use.

Warning

For external use only
Flammable - Keep away from fire or flame
When using this product, avoid contact with eyes. In case of
eye contact, rinse with water to remove.
Stop use and ask a doctor if irritation and redness develop.

Keep out of reach of children. If swallowed, get medical help
or contact a Poison Control Center right away.

Directions

. Wet hands thoroughly with product and allow to dry without wiping.

Inactive ingredients

Aqua

PACKAGE LABEL

40PCS NDC 76906-007-01